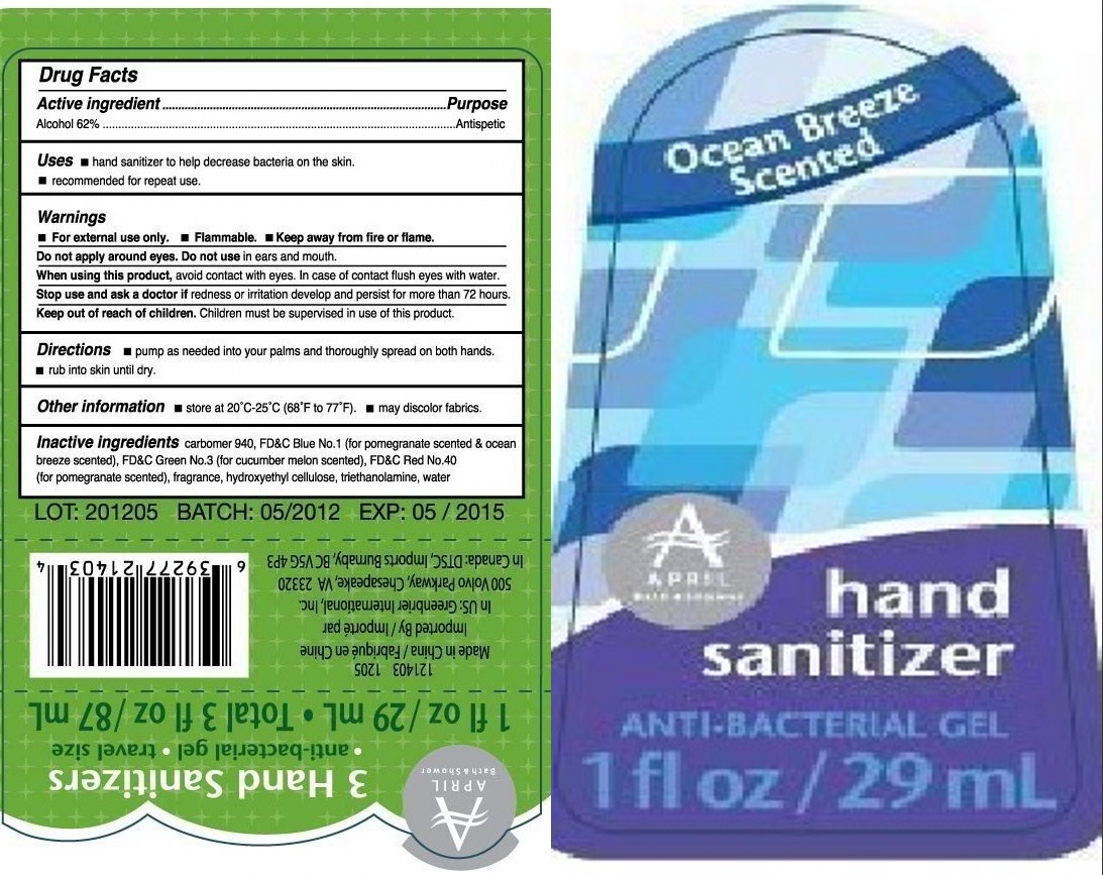 DRUG LABEL: Ocean Breeze Scented Hand Sanitizer
NDC: 33992-1205 | Form: GEL
Manufacturer: Greenbrier International
Category: otc | Type: HUMAN OTC DRUG LABEL
Date: 20120315

ACTIVE INGREDIENTS: alcohol 62 mL/100 mL
INACTIVE INGREDIENTS: CARBOMER HOMOPOLYMER TYPE C; FD&C BLUE NO. 1; HYDROXYETHYL CELLULOSE (140 CPS AT 5%); Water

Drug Fact

Active Ingredient Purpose
Alcohol 62% ********** Antiseptic

PURPOSE

Hand sanitizer to help decrease bacteria on the skin.
Recommended for repeat use

KEEP OUT OF REACH OF CHILDREN

Children must be supervised in use of this product.

INDICATIONS AND USAGE

Pump as needed into your palms and thoroughly spread on both hands.
Rub into skin until dry.

WARNINGS

Enter section text hereFor external use only.
Flammable, keep away from fire or flame.
Do not apply around eyes; Do not use in ears and mouth.
When using this products, avoid contact with eyes. In case of contact, flush eyes with water.
Stop use and ask a doctor, if redness or irritation develop and persist for more than 72 hours.

DOSAGE AND ADMINISTRATION

Pump as needed into your palms and thoroughly spread on both hands.
Rub into skin until dry.

INACTIVE INGREDIENT

Carbomer 940, FD+C Blue No. 1, Fragrance, Hydroxyethyl Cellulose, Triethanolamine, Water